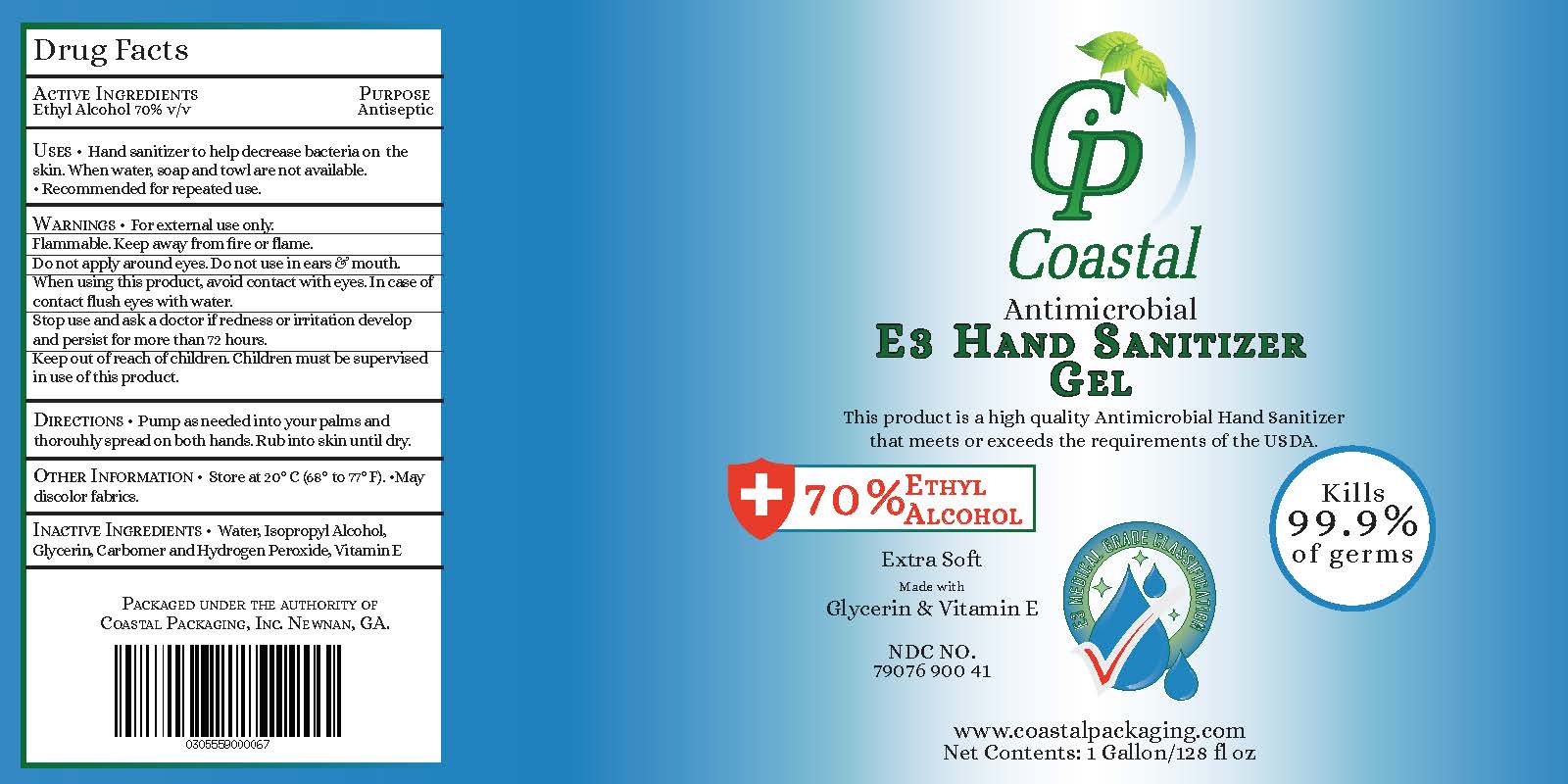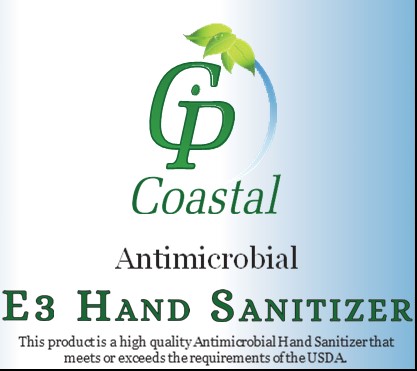 DRUG LABEL: Coastal Hand Sanitizer Gel
NDC: 79076-900 | Form: GEL
Manufacturer: U.S. BEVERAGE, INC.
Category: otc | Type: HUMAN OTC DRUG LABEL
Date: 20200804

ACTIVE INGREDIENTS: ALCOHOL 2649.5 mL/3785 mL
INACTIVE INGREDIENTS: CARBOMER 940 151.4 mL/3785 mL; ISOPROPYL ALCOHOL 113.55 mL/3785 mL; ALPHA-TOCOPHEROL 11.355 mL/3785 mL; GLYCERIN 287.66 mL/3785 mL; HYDROGEN PEROXIDE 37.85 mL/3785 mL; WATER 533.685 mL/3785 mL

Coasstal Hand Sanitizer Gel hand sanitizer is manufactured using only the following United States Pharmacopoeia (USP) grade active ingredient in the preparation of the product (percentage in final product formulation)

1. Alcohol (ethanol) (USP or Food Chemical Codex (FCC) grade) (70%, volume/volume (v/v)) in an aqueous solution denatured according to Alcohol and Tobacco Tax and Trade Bureau regulations in 27 CFR part 20

Inactive Ingredients

1. Glycerol (7.6% v/v).
2. Isopropyl Alcohol ((0.3% v/v)
3. Hydrogen peroxide (0.1% v/v).
4. Carbomer (0.4%)
5. Vitamin E (0.3% v/v)
6. Sterile distilled water

Label Gallon Bottle with FDA Logo 1 gallon

Active Ingredient(s)

Alcohol 70% v/v. Purpose: Antiseptic

Purpose

Antiseptic, Hand Sanitizer

Use

Hand Sanitizer to help reduce bacteria that potentially can cause disease. For use when soap and water are not available.

Warnings

For external use only. Flammable. Keep away from heat or flame

Do not use

- in children less than 2 months of age
- on open skin wounds

When using this product keep out of eyes, ears, and mouth. In case of contact with eyes, rinse eyes thoroughly with water.
Stop use and ask a doctor if irritation or rash occurs. These may be signs of a serious condition.
Keep out of reach of children. If swallowed, get medical help or contact a Poison Control Center right away.

Stop use and ask a doctor if irritation or rash occurs. These may be signs of a serious condition.

Keep out of reach of children. If swallowed, get medical help or contact a Poison Control Center right away.

Directions

- Place enough product on hands to cover all surfaces. Rub hands together until dry.
- Supervise children under 6 years of age when using this product to avoid swallowing.

Other information

- Store between 15-30C (59-86F)
- Avoid freezing and excessive heat above 40C (104F)

Inactive ingredients

glycerin, hydrogen peroxide, Isopropyl Alchol, Carbomer, Vitamin E, and purified water USP

Package Label - Principal Display Panel

3785 mL NDC: 79076-900-41

Label Gallon Bottle with FDA Logo 1 gallon

Label Gallon Bottle with FDA Logo 1 gallon Drug Facts